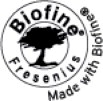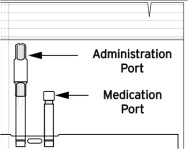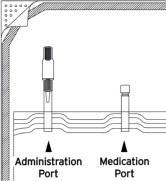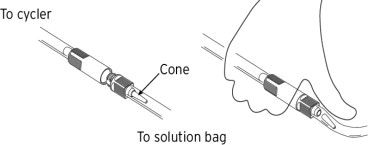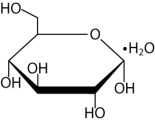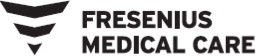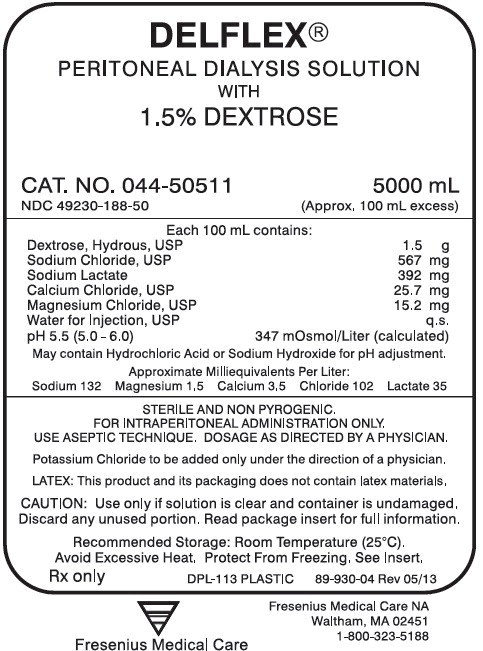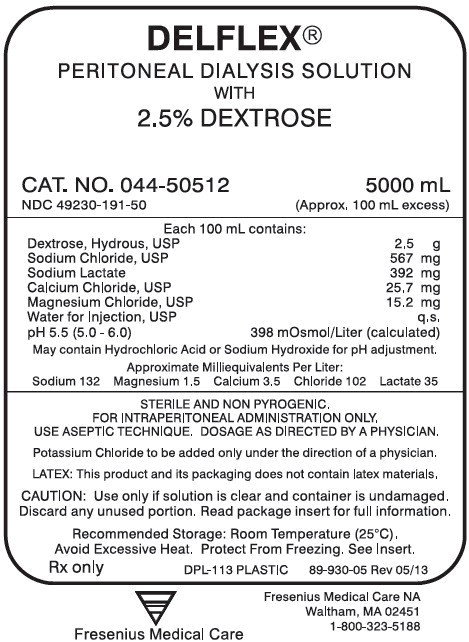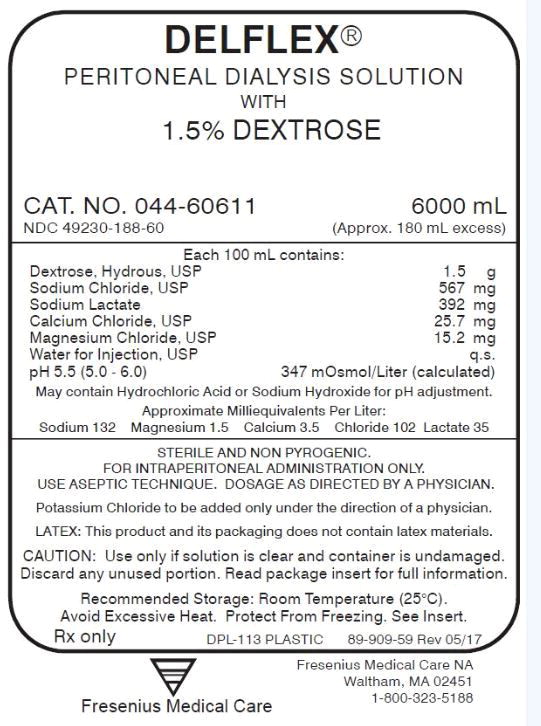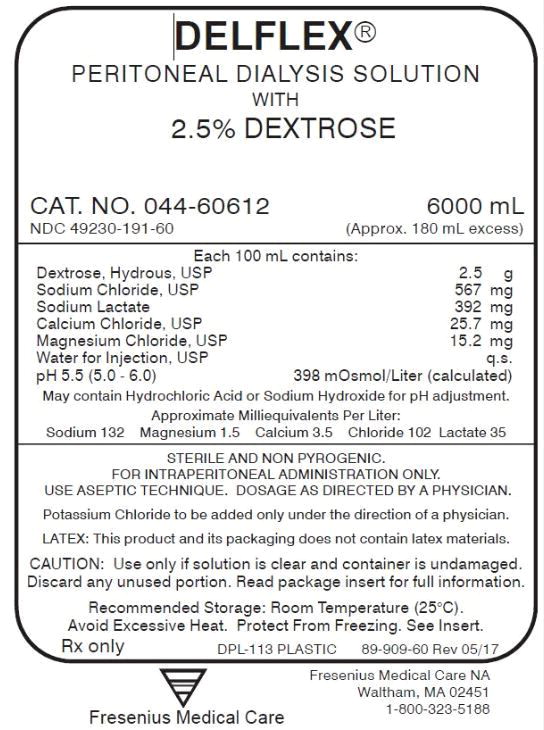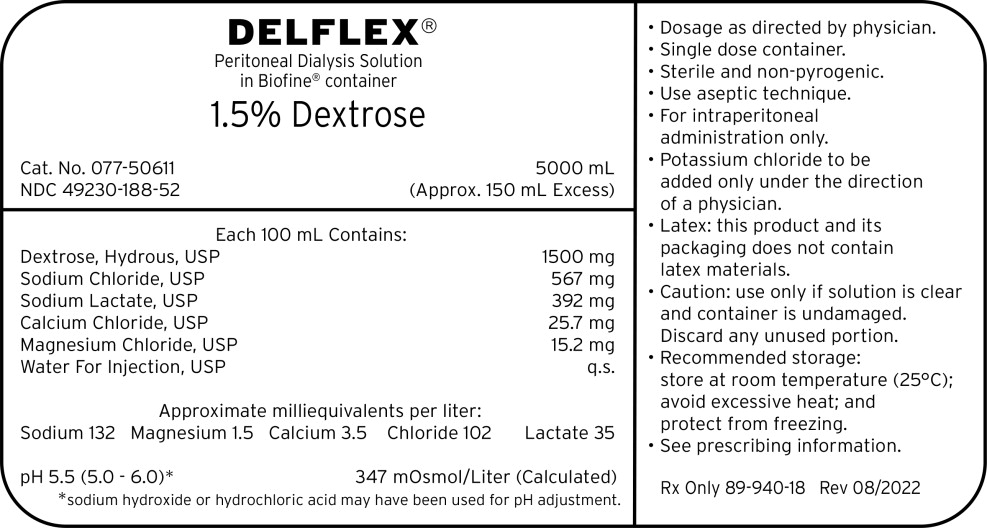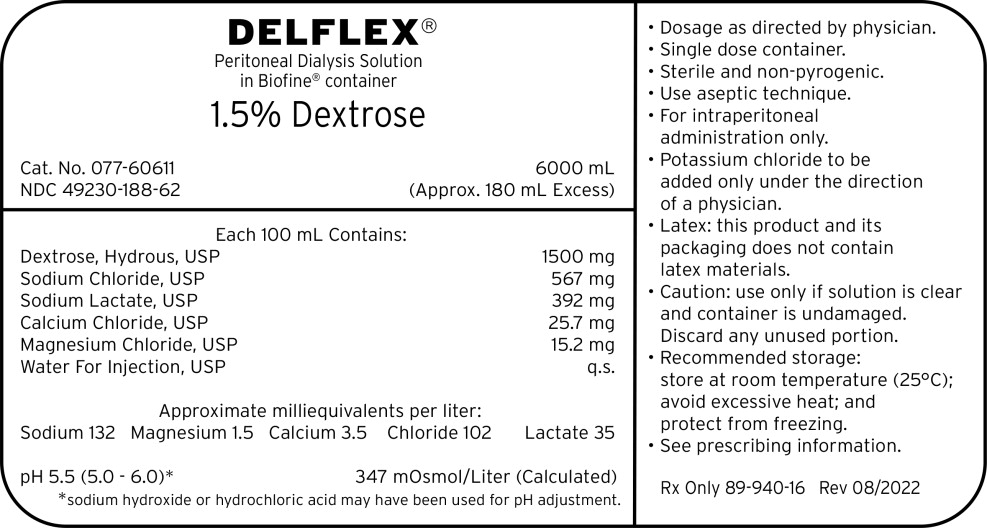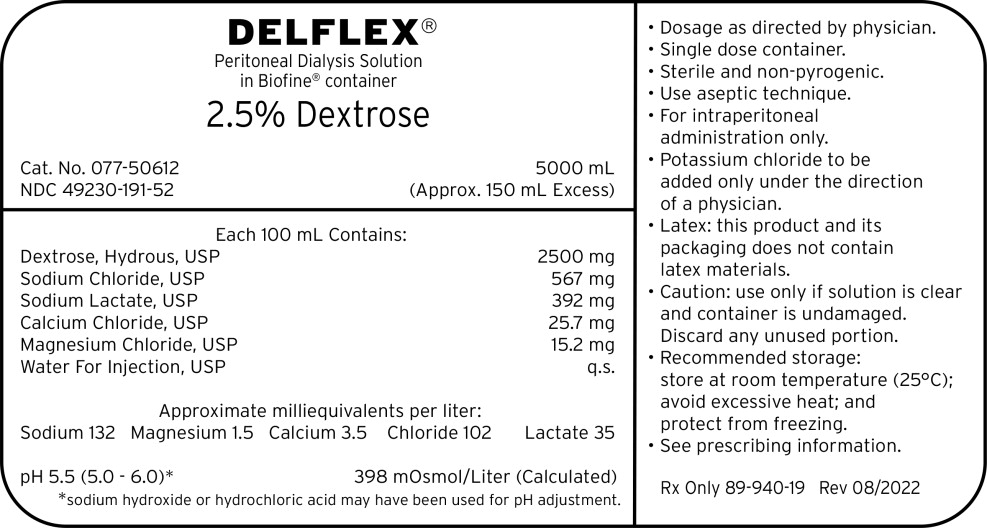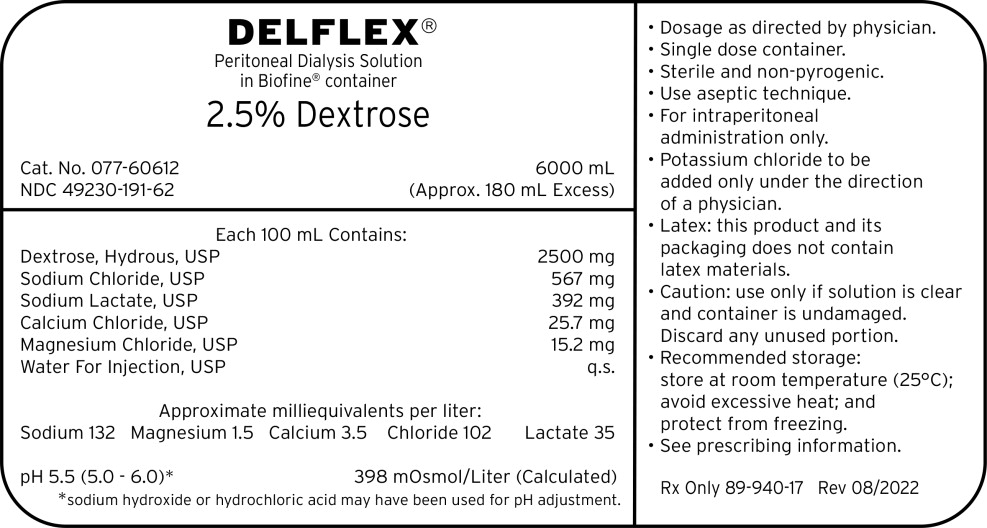 DRUG LABEL: DELFLEX
NDC: 49230-191 | Form: SOLUTION
Manufacturer: Fresenius Medical Care North America
Category: prescription | Type: HUMAN PRESCRIPTION DRUG LABEL
Date: 20251114

ACTIVE INGREDIENTS: SODIUM LACTATE
 392 mg/100 mL; CALCIUM CHLORIDE
 25.7 mg/100 mL; MAGNESIUM CHLORIDE
 15.2 mg/100 mL; DEXTROSE MONOHYDRATE
 2.5 g/100 mL; SODIUM CHLORIDE
 567 mg/100 mL
INACTIVE INGREDIENTS: WATER

HIGHLIGHTS OF PRESCRIBING INFORMATION

These highlights do not include all the information needed to use DELFLEX® safely and effectively. See full prescribing information for DELFLEX®
DELFLEX (dextrose) peritoneal dialysis solution
Initial U.S. Approval: 1984
DELFLEX Low Magnesium, Low Calcium (dextrose) peritoneal dialysis solution
Initial U.S. Approval: 1992

1. INDICATIONS AND USAGE

For treatment of chronic kidney failure. (1)

2. DOSAGE AND ADMINISTRATION

For intraperitoneal dialysis only. (2)

3. DOSAGE FORMS AND STRENGTHS

DELFLEX solutions are available in multiple compositions, calculated osmolarity, pH, and ionic concentrations. See full prescribing information for detailed descriptions of each formulation. (3, 11)

4. CONTRAINDICATIONS

None

5. WARNINGS AND PRECAUTIONS

- Monitor patient for electrolyte, fluid, and nutrition imbalances. (5.1)
- Encapsulating Peritonitis Sclerosis (EPS) (5.2)
- Peritonitis: Initiate appropriate antimicrobial therapy (5.2)
- Monitor for Lactic Acidosis in patients at risk. (5.3)

6. ADVERSE REACTIONS

Adverse reactions may include peritonitis, catheter site infection, electrolyte and fluid imbalances, hypovolemia, hypervolemia, hypertension, disequilibrium syndrome, muscle cramping, abdominal pain, abdominal distension, and abdominal discomfort. (6)

To report SUSPECTED ADVERSE REACTIONS, contact Fresenius Medical Care North America at 1-800-323-5188 or FDA at 1-800-FDA-1088 or www.fda.gov/medwatch.

FULL PRESCRIBING INFORMATION

1. INDICATIONS AND USAGE

DELFLEX® is indicated in the treatment of chronic kidney failure in patients being maintained on peritoneal dialysis.

2. DOSAGE AND ADMINISTRATION

2.1 Basic Dosing Information

DELFLEX® is intended for intraperitoneal administration only. Not for intravenous or intra-arterial administration.

The mode of therapy, frequency of treatment, formulation, exchange volume, duration of dwell, and length of dialysis should be selected by the physician responsible for the treatment of the individual patient.

Utilize the peritoneal dialysis solution with lowest level of osmolarity consistent with the fluid removal requirements for that exchange.

Do not store solutions containing additives.

2.2 Administration Instructions

Parenteral drug products should be inspected visually for particulate matter and discoloration prior to administration whenever solution and container permit.

Do not heat in a microwave oven.

Get Ready

1. Clean work surface.
2. Gather supplies:
  - DELFLEX peritoneal dialysis bag(s).
  - Prescribed medication(s), if ordered by your healthcare provider.
  - Mask.
3.
  PVC
  Tear the overwrap from the slit edge down the length of the inner bag to open. | Locate pull tabs on overwrap. Grasping one tab in each hand, pull outward, down the length of the inner bag to open.
  Wipe away any moisture from the solution bags. Some opacity may be observed in the plastic of the bag and/or tubing and is due to moisture absorption during the sterilization process. This is normal and does not affect the solution quality or safety. The opacity will diminish gradually. | Wipe away any moisture from the solution bags.
  Inspect DELFLEX Solution Bag
4. After removing the overwrap, check your DELFLEX solution bag(s) for strength, clarity, amount, leaks, and expiration date. Do not use DELFLEX solution if leaks are found, the solution bag is damaged, and/or the solution is cloudy or discolored, or the product is expired. Color may vary from clear to slightly yellow but does not affect efficacy and may be used.
5. Visually check that the solution bag tubing is free from kinks. If kinks are present, straighten tubing to allow the solution to flow freely.
  Note: Retain DELFLEX peritoneal dialysis bag sample for manufacturer evaluation and notify your healthcare provider if any of the above defects are found.
  Note: DELFLEX peritoneal dialysis solutions utilize the Safe-Lock® Connection System. This unique system consists of two Safe-Lock connectors, one located on the administration port of the bag, and the mating connector is located on the cycler set. The Safe-Lock connectors were designed to reduce the potential risk of touch contamination of the internal connection components.
6. Put on mask. Wash your hands.
7. If you will be adding medications(s):
  - Clean hands (as per facility's protocol)
  - Clean the medication port as instructed by your healthcare provider.
  - Add the medicine(s).
  - Turn the bag upside down several times to mix the medicine(s).
8. To connect the bag(s) to the cycler set, unscrew the protective caps of the administration port and the cycler set solution line connector. Secure these two connectors with a twisting motion to lock in place, so that the cycler set connector is seated over the administration port O-ring to assure a firm and tight fit.
9. After completing Step 8, wait for the cycler prompt to break the administration port cone and initiate solution flow. Do this by placing the thumb firmly on the tube over the cone and pressing towards the outer wall of the tube and away from the bag.
10. Perform your treatment as prescribed.
11. At the end of your treatment, throw away the fluid and used set as instructed by your healthcare provider. In case of cloudiness, save the fluid and the used set and immediately contact your healthcare provider. Dispose of your empty solution bag according to your local recycling program. Empty solution bags may not be recyclable in your area.

2.3 Compatible Medications

Compatible medications can be added via the medication port [see Dosage and Administration (2.2)]. The following medications have demonstrated stability with DELFLEX solutions: cefazolin, ceftazidime, gentamicin, and vancomycin [see Clinical Pharmacology (12.3)] .

3. DOSAGE FORMS AND STRENGTHS

DELFLEX peritoneal dialysis solutions are available in single-dose flexible bags comprised of either polyvinyl chloride (PVC), or a proprietary blend of polyolefins called Biofine®. All DELFLEX peritoneal dialysis solutions have overfills declared on the bag label.

DELFLEX peritoneal dialysis solutions are available in the sizes and formulations shown in Table 1.

Table 1. DELFLEX peritoneal dialysis solution sizes and formulations
 | PVC |  |  |  | Biofine®
 | 2L | 3L | 5L | 6L | 3L | 5L | 6L
DELFLEX Standard with 1.5% Dextrose |  |  | X | X |  | X | X
DELFLEX Standard with 2.5% Dextrose |  |  | X | X |  | X | X
DELFLEX Low Magnesium, Low Calcium with 1.5% Dextrose | X | X | X | X | X | X | X
DELFLEX Low Magnesium, Low Calcium with 2.5% Dextrose | X | X | X | X | X | X | X
DELFLEX Low Magnesium, Low Calcium with 4.25% Dextrose | X | X | X | X | X | X | X

4. CONTRAINDICATIONS

None.

5. WARNINGS AND PRECAUTIONS

5.1 Electrolyte, Fluid and Nutrition Imbalances

Peritoneal dialysis may affect a patient's protein, water-soluble vitamin, potassium, sodium, chloride, bicarbonate, and magnesium levels and volume status. Monitor electrolytes and blood chemistry periodically and take appropriate clinical action.

Potassium is omitted from DELFLEX solutions because dialysis may be performed to correct hyperkalemia. In situations where there is a normal serum potassium level or hypokalemia, the addition of potassium chloride (up to a concentration of 4 mEq/L) may be indicated to prevent severe hypokalemia.

To avoid the risk of severe dehydration or hypovolemia and to minimize the loss of protein, it is advisable to select the peritoneal dialysis solution with lowest level of osmolarity consistent with the fluid removal requirements for that exchange.

Significant loss of protein, amino acids and water-soluble vitamins may occur during peritoneal dialysis. Replacement therapy should be provided as necessary.

5.2 Peritonitis and Encapsulating Peritoneal Sclerosis

Infectious and aseptic peritonitis has been associated with peritoneal dialysis therapy. Following DELFLEX use, inspect the drained fluid for the presence of fibrin or cloudiness, which may indicate the presence of peritonitis. Improper clamping or priming sequence may result in infusion of air into the peritoneal cavity, which may result in abdominal pain and/or peritonitis. If peritonitis occurs, treat with appropriate therapy.

Encapsulating peritoneal sclerosis (EPS), sometimes fatal, is a complication of peritoneal dialysis therapy.

5.3 Lactic Acidosis

Monitor patients with conditions known to increase the risk of lactic acidosis [e.g., severe hypotension or sepsis that can be associated with acute kidney failure, inborn errors of metabolism, treatment with drugs such as nucleoside/nucleotide reverse transcriptase inhibitors (NRTIs)] for lactic acidosis before the start of treatment and during treatment with DELFLEX.

Solutions containing the lactate ion should be used with great care in patients with metabolic or respiratory alkalosis. Lactate should be administered with great care in those conditions in which there is an increased level or an impaired utilization of this ion, such as severe hepatic insufficiency.

5.4 Over Infusion

Over infusion of peritoneal dialysis solution volume into the peritoneal cavity may be characterized by abdominal distention, feeling of fullness and/or shortness of breath. Drain the peritoneal dialysis solution from the peritoneal cavity to treat over infusion.

6. ADVERSE REACTIONS

Solution related adverse reactions may include peritonitis, catheter site infection, electrolyte and fluid imbalances, hypovolemia, hypervolemia, hypertension, hypotension, disequilibrium syndrome, muscle cramping, abdominal pain, abdominal distension, and abdominal discomfort.

8. USE IN SPECIFIC POPULATIONS

8.1 Pregnancy

Risk Summary

DELFLEX solutions consist of electrolytes, lactate, and bicarbonate at physiological levels, and glucose to facilitate ultrafiltration. While there are no adequate and well controlled studies in pregnant women, appropriate administration of DELFLEX with monitoring of fluid, electrolyte, acid-base and glucose balance, is not expected to cause fetal harm. Animal reproduction studies have not been conducted with DELFLEX.

The estimated background risk of major birth defects and miscarriage for the indicated population are unknown. All pregnancies have a background risk of birth defect, loss or other adverse outcomes. In the U.S. general population, the estimated background risk of major birth defects and miscarriage in clinically recognized pregnancies is 2 to 4% and 15 to 20%, respectively.

8.2 Lactation

Risk Summary

The components of DELFLEX solutions are excreted in human milk. Appropriate administration of DELFEX solutions with monitoring of fluid, electrolyte, acid-base and glucose balance, is not expected to harm a nursing infant.

8.4 Pediatric Use

Safety and effectiveness in pediatric patients have not been established.

11. DESCRIPTION

The DELFLEX® peritoneal dialysis solutions (standard and low magnesium/low calcium) are sterile, non-pyrogenic formulations of dextrose and electrolytes in water for injection, USP, for use in peritoneal dialysis. These solutions do not contain antimicrobial agents or additional buffers. Composition, calculated osmolarity, pH, and ionic concentrations are shown in Table 2.

Table 2. Composition, calculated osmolarity, pH and ionic concentration
 | Composition/100mL |  |  |  |  | Total Osmolarity (mOsmoL/L) (calc) | pH (5.0 - 6.0) | Ionic Concentration (mEq/L)
 | Dextrose Hydrous, USP (C6H12O6⋅H2O) | Sodium Chloride. USP (NaCI) | Sodium Lactate (C3H5NaO3) | Calcium Chloride, USP (CaCl2⋅2H2O) | Magnesium Chloride, USP (MgCl2-6H20) | Total Osmolarity (mOsmoL/L) (calc) | pH (5.0 - 6.0) | Sodium | Calcium | Magnesium | Chloride | Lactate
DELFLEX Standard with 1.5% Dextrose | 1.5 g | 567 mg | 392 mg | 25.7 mg | 15.2 mg | 347 | 5.5 | 132 | 3.5 | 1.5 | 102 | 35
DELFLEX Standard with 2.5% Dextrose | 2.5 g | 567 mg | 392 mg | 25.7 mg | 15.2 mg | 398 | 5.5 | 132 | 3.5 | 1.5 | 102 | 35
DELFLEX Low Magnesium, Low Calcium with 1.5% Dextrose | 1.5 g | 538 mg | 448 mg | 18.4 mg | 5.08 mg | 344 | 5.5 | 132 | 2.5 | 0.5 | 95 | 40
DELFLEX Low Magnesium, Low Calcium with 2.5% Dextrose | 2.5 g | 538 mg | 448 mg | 18.4 mg | 5.08 mg | 394 | 5.5 | 132 | 2.5 | 0.5 | 95 | 40
DELFLEX Low Magnesium, Low Calcium with 4.25% Dextrose | 4.25g | 538 mg | 448 mg | 18.4 mg | 5.08 mg | 483 | 5.5 | 132 | 2.5 | 0.5 | 95 | 40

Dextrose, USP, is chemically designated D-glucose monohydrate (C6H12O6•H2O) a hexose sugar freely soluble in water. The structural formula is shown here:

Calcium chloride, USP, is chemically designated calcium chloride dihydrate (CaCl2•2H2O) white fragments or granules freely soluble in water.

Magnesium chloride, USP, is chemically designated magnesium chloride hexahydrate (MgCl2 •6H2O) colorless flakes or crystals very soluble in water.

Sodium lactate solution, USP, is chemically designated (CH3CH(OH)COONa), a 60% aqueous solution miscible in water.

Sodium chloride, USP, is chemically designated (NaCl), a white, crystalline compound freely soluble in water.

Water for injection, USP, is chemically designated (H2O).

Hydrochloric Acid or Sodium Hydroxide may be added for pH adjustment. pH is 5.5 ± 0.5.

Exposure to temperatures above 25°C (77°F) during transport and storage will lead to minor losses in moisture content. Higher temperatures lead to greater losses. It is unlikely that these minor losses will lead to clinically significant changes within the expiration period. Since the inner bag is compounded from flexible plastic, water may permeate from the inner bag into the overwrap in quantities insufficient to affect the solution significantly. Solutions in contact with the plastic inner bag can cause certain chemical components of the bag to leach out in very small amounts; however, the safety of the plastic formulation is supported by biological tests for plastic containers.

12. CLINICAL PHARMACOLOGY

12.1 Mechanism of Action

DELFLEX peritoneal dialysis solutions are hypertonic peritoneal dialysis solutions containing dextrose, a monosaccharide, as the primary osmotic agent. An osmotic gradient must be created between the peritoneal membrane and the dialysis solution in order for ultrafiltration to occur. The hypertonic concentration of glucose in DELFLEX solutions exert an osmotic pressure across the peritoneal membrane resulting in transcapillary ultrafiltration. Like other peritoneal dialysis solutions, DELFLEX solutions contain electrolytes to facilitate the correction of acid-base and electrolyte abnormalities. DELFLEX solutions contain a buffer, lactate, to help normalize acid-base abnormalities.

12.3 Pharmacokinetics

Absorption

Glucose can be rapidly absorbed from the peritoneal cavity by diffusion and appears quickly in the circulation due to the high glucose concentration gradient between DELFLEX solutions compared to blood capillary glucose level. Absorption per unit time will be the highest at the start of an exchange and decreases over time. The rate of glucose absorption will be dependent upon the transport characteristics of the patient's peritoneal membrane as determined by a peritoneal equilibration test (PET). Glucose absorption will also depend upon the concentration of glucose used for the exchange and the length of the dwell. Transport of other molecules will be dependent upon the molecular size of the solute, the concentration gradient, and the effective peritoneal surface area as determined by the PET.

Metabolism and Elimination

Glucose is metabolized by normal cellular pathways (i.e., glycolysis). Metabolism of lactate occurs in the liver and results in the generation of the bicarbonate. Glucose not absorbed during PD exchange procedure is removed by drainage of the PD solution from the peritoneal cavity.

Drug Interaction Studies

Antibiotics

No formal clinical drug interaction studies have been performed. In vitro studies of the following medications have demonstrated stability with DELFLEX solutions: cefazolin, ceftazidime, gentamicin, and vancomycin.

13. NONCLINICAL TOXICOLOGY

13.1 Carcinogenesis, Mutagenesis, Impairment of Fertility

Long term animal studies with DELFLEX peritoneal dialysis solutions have not been performed to evaluate the carcinogenic potential, mutagenic potential or effect on fertility.

16. HOW SUPPLIED/STORAGE AND HANDLING

DELFLEX peritoneal dialysis solutions are available in the sizes and formulations shown in Table 1 [see Dosage Forms and Strengths (3)] .

Table 3. DELFLEX peritoneal dialysis NDC designations
 | PVC |  |  |  | Biofine®
 | 2L | 3L | 5L | 6L | 3L | 5L | 6L
Standard 1.5% Dextrose |  |  | 49230- 188-50 | 49230- 188-60 |  | 49230- 188-52 | 49230- 188-62
Standard 2.5% Dextrose |  |  | 49230- 191-50 | 49230- 191-60 |  | 49230- 191-52 | 49230- 191-62
Low Mg/Low Ca 1.5% Dextrose | 49230- 206-20 | 49230- 206-30 | 49230- 206-50 | 49230- 206-60 | 49230- 206-32 | 49230- 206-52 | 49230- 206-62
Low Mg/Low Ca 2.5% Dextrose | 49230- 209-23 | 49230- 209-30 | 49230- 209-50 | 49230- 209-60 | 49230- 209-32 | 49230- 209-52 | 49230- 209-62
Low Mg/Low Ca 4.25% Dextrose | 49230- 212-23 | 49230- 212-30 | 49230- 212-50 | 49230- 212-60 | 49230- 212-32 | 49230- 212-52 | 49230- 212-62

Store at 20°C to 25°C (68°F to 77°F); excursions permitted between 15°C and 30°C (between 59°F and 86°F). See USP Controlled Room Temperature. Brief exposure to temperatures up to 40°C (104°F) may be tolerated provided the mean kinetic temperature does not exceed 25°C (77°F); however, such exposure should be minimized.

Keep DELFLEX and all medicines out of the reach of children.

17. PATIENT COUNSELING INFORMATION

Aseptic technique must be used throughout the procedure and at its termination in order to reduce the possibility of infection.

The solution bag should remain in the carton and the overwrap intact until time of use.

Use only after checking for strength, clarity, amount, leaks, and expiration date.

Advise patients that DELFLEX peritoneal dialysis solution should not be heated in a microwave oven.

Care should be taken to ensure that there is not any leakage around the catheter, since if not controlled, the leakage can create edema from subcutaneous infiltration of the dialysis solution. The leakage will also create an inaccurate fluid balance measurement. If any leakage is identified, advise the patient not to proceed with infusion and notify your physician.

Fresenius Medical Care North America
920 Winter Street
Waltham, MA 02451
1-800-323-5188

© 2020, 2022 Fresenius Medical Care. All Rights Reserved. Fresenius Medical Care, triangle logo, DELFLEX, Safe-Lock, Biofine are trademarks of Fresenius Medical Care Holding, Inc. or affiliated companies.

PACKAGE LABEL

Principal Display Panel – 1.5% Dextrose 5000 mL Bag Label

DELFLEX®

PERITONEAL DIALYSIS SOLUTION
WITH
1.5% DEXTROSE

CAT. NO. 044-50511

NDC 49230-188-50

5000 mL
(Approx. 100 mL excess)

PACKAGE LABEL

Principal Display Panel – 2.5% Dextrose 5000 mL Bag Label

DELFLEX®

PERITONEAL DIALYSIS SOLUTION
WITH
2.5% DEXTROSE

CAT. NO. 044-50512

NDC 49230-188-50

5000 mL
(Approx. 100 mL excess)

PACKAGE LABEL

Principal Display Panel – 1.5% Dextrose 6000 mL Bag Label

DELFLEX®

PERITONEAL DIALYSIS SOLUTION
WITH
1.5% DEXTROSE

CAT. NO. 044-60611

NDC 49230-188-60

6000 mL
(Approx. 180 mL excess)

PACKAGE LABEL

Principal Display Panel – 2.5% Dextrose 6000 mL Bag Label

DELFLEX®

PERITONEAL DIALYSIS SOLUTION
WITH
2.5% DEXTROSE

CAT. NO. 044-60612

NDC 49230-191-60

6000 mL
(Approx. 180 mL excess)

PACKAGE LABEL

Principal Display Panel – 1.5% Dextrose 5000 mL Bag Label

DELFLEX®

Peritoneal Dialysis Solution
in Biofine® container

1.5% Dextrose

Cat. No. 077-50611

NDC 49230-188-52

5000 mL
(Approx. 150 mL Excess)

PACKAGE LABEL

Principal Display Panel – 1.5% Dextrose 6000 mL Bag Label

DELFLEX®

Peritoneal Dialysis Solution
in Biofine® container

1.5% Dextrose

Cat. No. 077-60611

NDC 49230-188-62

6000 mL
(Approx. 180 mL Excess)

PACKAGE LABEL

Principal Display Panel – 2.5% Dextrose 5000 mL Bag Label

DELFLEX®

Peritoneal Dialysis Solution
in Biofine® container

2.5% Dextrose

Cat. No. 077-50612

NDC 49230-191-52

5000 mL
(Approx. 150 mL Excess)

PACKAGE LABEL

Principal Display Panel – 2.5% Dextrose 6000 mL Bag Label

DELFLEX®

Peritoneal Dialysis Solution
in Biofine® container

2.5% Dextrose

Cat. No. 077-60612

NDC 49230-191-62

6000 mL
(Approx. 180 mL Excess)